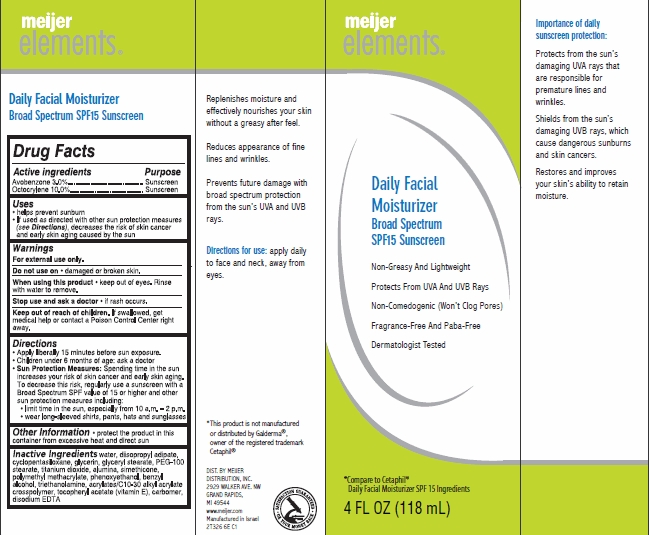 DRUG LABEL: Meijer Elements Daily Facial Moisturizer
NDC: 41250-326 | Form: CREAM
Manufacturer: Meijer Distribution Inc
Category: otc | Type: HUMAN OTC DRUG LABEL
Date: 20130110

ACTIVE INGREDIENTS: AVOBENZONE 3 g/100 mL; OCTOCRYLENE 10 g/100 mL
INACTIVE INGREDIENTS: WATER; DIISOPROPYL ADIPATE; CYCLOMETHICONE 5; GLYCERIN; GLYCERYL 1-STEARATE; PEG-100 STEARATE; TITANIUM DIOXIDE; ALUMINUM HYDROXIDE; DIMETHICONE; POLY(METHYL ACRYLATE-CO-METHYL METHACRYLATE-CO-METHACRYLIC ACID 7:3:1; 280000 MW); PHENOXYETHANOL; BENZYL ALCOHOL; TROLAMINE; CARBOMER HOMOPOLYMER TYPE C (ALLYL PENTAERYTHRITOL CROSSLINKED); .ALPHA.-TOCOPHEROL ACETATE; CARBOMER COPOLYMER TYPE A (ALLYL PENTAERYTHRITOL CROSSLINKED); EDETATE DISODIUM

meijer elements® Daily Facial Moisturizer

Active ingredient

Avobenzone 3.0%

Octocrylene 10.0%

Purpose

Sunscreen

Keep Out of Reach of Children

If swallowed, get medical help or contact a Poison Control Center right away.

Uses

help prevent sunburn

If used as directed with other sun protection measures (see Directions), decreases the risk of skin cancer and early skin aging caused by the sun

Warnings

For external use only.

Do not use on damaged or broken skin.

When using this product keep out of eyes. Rinse with water to remove.

Stop use and ask a doctor if rash occurs.

Directions

Apply liberally 15 minutes before sun exposure.

Children under 6 months of age: ask a doctor

Sun Protection Measures: Spending time in the sun increases your risk of skin cancer and early skin aging. To decrease this risk, regularly use a sunscreen with a Broad Spectrum SPF value of 15 or higher and other sun protection measures including:

limit time in the sun, especially from 10 a.m.-2 p.m.

wear long-sleeved shirts, pants, hats and sunglasses

Inactive ingredients

water, diisopropyl adipate, cyclopentasiloxane, glycerin, glyceryl stearate, PEG-100 stearate, titanium dioxide, alumina, simethicone, polymethyl methacrylate, phenoxyethanol, benzyl alcohol, triethanolamine, acrylates/C10-30 alkyl acrylate crosspolymer, tocopheryl acetate (vitamin E), carbomer, disodium EDTA

Package/Label Principal Display Panel

meijer elements® Daily Facial Moisturizer

Broad Spectrum SPF15 Sunscreen

- non-greasy and lightweight
- protects from UVA and UVB rays
- non-comedogenic (won't clog pores)
- fragrance-free and paba-free
- dermatologist tested

4 FL OZ (118 mL)

DISTRIBUTED BY:
MEIJER DISTRIBUTION, INC.
2929 WALKER AVE. NW
GRAND RAPIDS,
MI 49544
www.meijer.com
Manufactured in Israel
2T326 6E C1

Carton Label